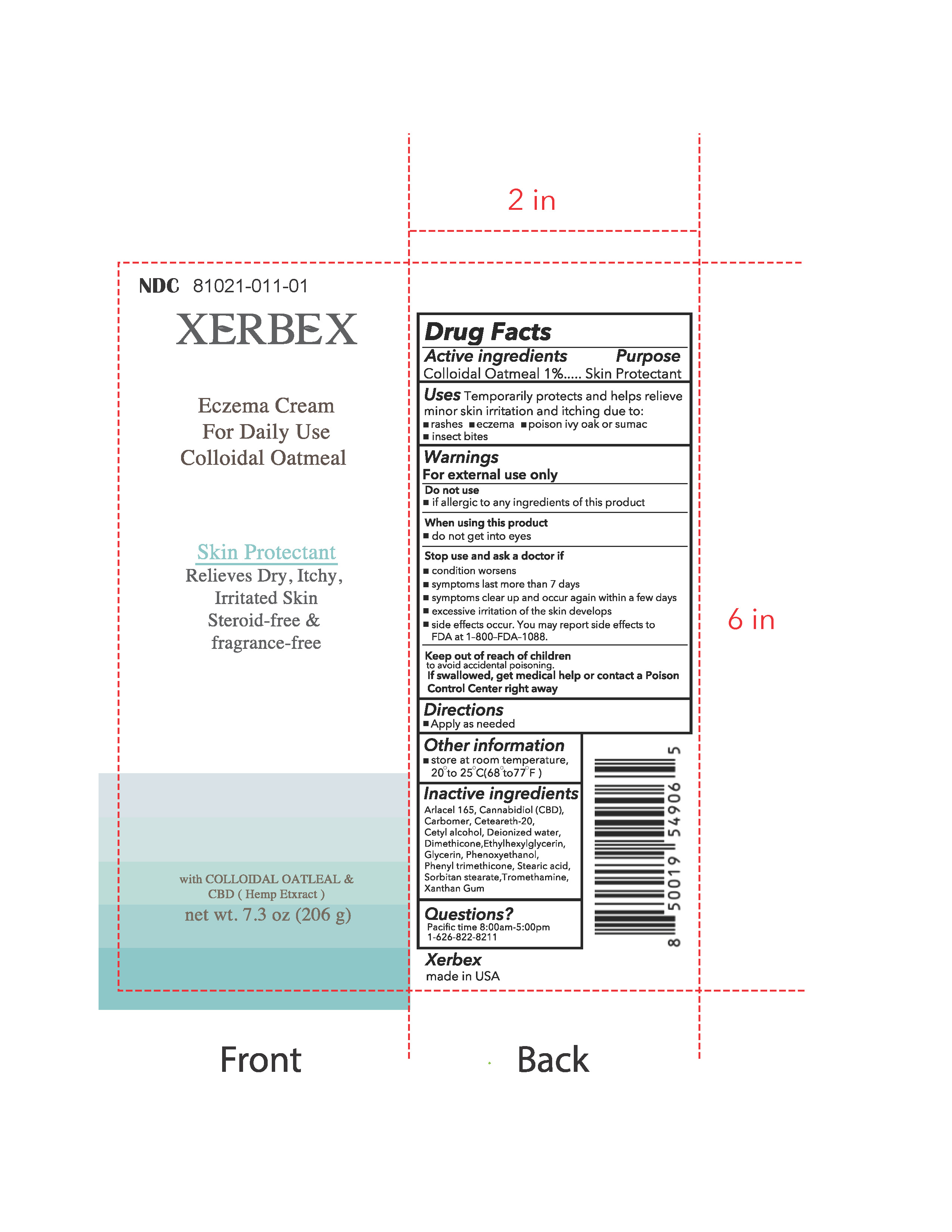 DRUG LABEL: Xerbex Eczema Cream
NDC: 81021-011 | Form: CREAM
Manufacturer: Xerbal USA LLC
Category: otc | Type: HUMAN OTC DRUG LABEL
Date: 20210402

ACTIVE INGREDIENTS: OATMEAL 1 g/100 g
INACTIVE INGREDIENTS: GLYCERYL STEARATE/PEG-100 STEARATE; CANNABIDIOL; CARBOMER HOMOPOLYMER, UNSPECIFIED TYPE; POLYOXYL 20 CETOSTEARYL ETHER; CETYL ALCOHOL; WATER; DIMETHICONE; ETHYLHEXYLGLYCERIN; GLYCERIN; PHENOXYETHANOL; PHENYL TRIMETHICONE; STEARIC ACID; SORBITAN MONOSTEARATE; TROMETHAMINE; XANTHAN GUM

Xerbex Eczema Cream

Drug Facts

ACTIVE INGREDIENT

Active Ingredients | Purpose
Colloidal Oatmeal 1% | Skin Protectant

Uses

Temporarily protects and helps relieve minor skin irritation and itching due to:

- rashes
- eczema
- poison ivy, oak, or sumac
- insect bites

Warnings

For external use only

Do not use

- if allergic to any ingredients of this product

When using this product

- do not get into eyes

Stop use and ask a doctor if

- condition worsens
- symptoms last more than 7 days
- symptoms clear up and occur again within a few days
- excessive irritation of the skin develops
- side effects occur. You may report side effects to FDA at 1–800–FDA–1088.

Keep out of reach of children to avoid accidental poisoning .

If swallowed, get medical help or contact a Poison Control Center right away.

Directions

- Apply as needed

Other information

- store at room temperature, 20 to 25 oC(68 to 77oF)

Inactive ingredients

Arlacel 165, Cannabidiol (CBD), Carbomer, Ceteareth-20, Cetyl alcohol, Deionized water, Dimethicone, Ethylhexylglycerin, Glycerin, Phenoxyethanol, Phenyl trimethicone, Stearic acid, Sorbitan stearate, Tromethamine, Xanthan Gum

Questions?

Pacific Time 8:00am to 5:00pm

1-626-822-8211

PRINCIPAL DISPLAY PANEL - 7.3 oz (206 g)

NDC.No : 81021-011-01

Xerbex Eczema Cream

Skin Protectant

Xerbex